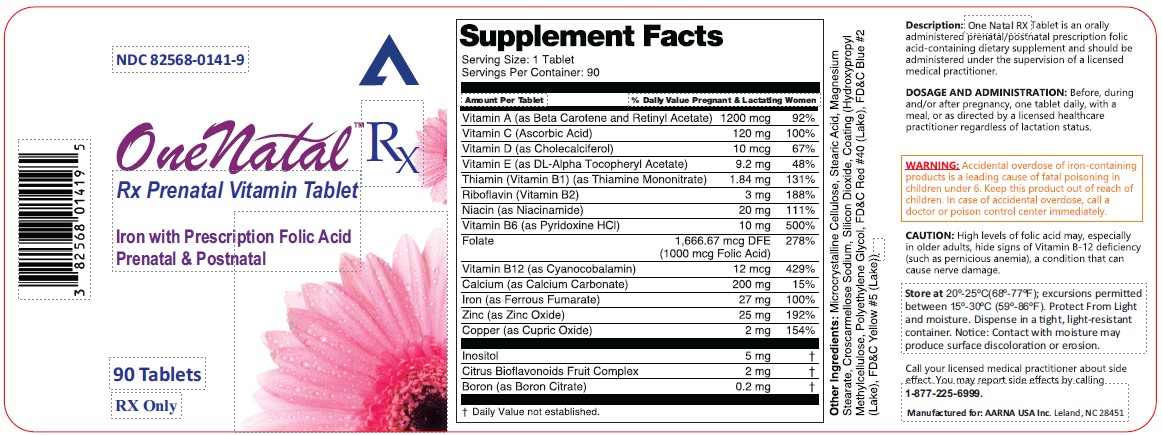 DRUG LABEL: One Natal Rx
NDC: 82568-0141 | Form: TABLET
Manufacturer: AARNA USA INC
Category: prescription | Type: HUMAN PRESCRIPTION DRUG LABEL
Date: 20250825

ACTIVE INGREDIENTS: VITAMIN A 1200 ug/1 1; ASCORBIC ACID 120 mg/1 1; VITAMIN D 10 ug/1 1; .ALPHA.-TOCOPHEROL ACETATE, DL- 9.2 mg/1 1; THIAMINE 1.84 mg/1 1; RIBOFLAVIN 3 mg/1 1; NIACINAMIDE 20 mg/1 1; PYRIDOXINE HYDROCHLORIDE 10 mg/1 1; FOLIC ACID 1666.67 ug/1 1; CYANOCOBALAMIN 12 ug/1 1; CALCIUM CARBONATE 200 mg/1 1; FERROUS FUMARATE 27 mg/1 1; ZINC OXIDE 25 mg/1 1; CUPRIC OXIDE 2 mg/1 1; INOSITOL 5 mg/1 1; CITRUS BIOFLAVONOIDS 2 mg/1 1; BORON CITRATE 0.2 mg/1 1
INACTIVE INGREDIENTS: MICROCRYSTALLINE CELLULOSE; STEARIC ACID; MAGNESIUM STEARATE; CROSCARMELLOSE SODIUM; SILICON DIOXIDE; HYDROXYPROPYL METHYLCELLULOSE; POLYETHYLENE GLYCOL, UNSPECIFIED; FD&C RED NO. 40; FD&C BLUE NO. 2; FD&C YELLOW NO. 5

OneNatalTM RX
Rx Prenatal Vitamin Tablet
Iron with Prescription Folic Acid
Prenatal & Postnatal

HEALTH CLAIM

Serving Size: 1 Tablet
Servings Per Container: 90
Amount Per Tablet | % Daily Value Pregnant & Lactating Women
Vitamin A (as Beta Carotene and Retinyl Acetate) | 1200 mcg | 92%
Vitamin C (Ascorbic Acid) | 120 mg | 100%
Vitamin D (as Cholecalciferol) | 10 mcg | 67%
Vitamin E (as DL-Alpha Tocopheryl Acetate) | 9.2 mg | 48%
Thiamin (Vitamin B1) (as Thiamine Mononitrate) | 1.84 mg | 131%
Riboflavin (Vitamin B2) | 3 mg | 188%
Niacin (as Niacinamide) | 20 mg | 111%
Vitamin B6 (as Pyridoxine HCl) | 10 mg | 500%
Folate | 1,666.67 mcg DFE (1000 mcg Folic Acid) | 278%
Vitamin B12 (as Cyanocobalamin) | 12 mcg | 429%
Calcium (as Calcium Carbonate) | 200 mg | 15%
Iron (as Ferrous Fumarate) | 27 mg | 100%
Zinc (as Zinc Oxide) | 25 mg | 192%
Copper (as Cupric Oxide) | 2 mg | 154%
Inositol | 5 mg | †
Citrus Bioflavonoids Fruit Complex | 2 mg | †
Boron (as Boron Citrate) | 0.2 mg | †
† Daily Value not established.

Other Ingredients: Microcrystalline Cellulose, Stearic Acid, Magnesium Stearate, Croscarmellose Sodium, Silicon Dioxide, Coating (Hydroxypropyl Methylcellulose, Polyethylene Glycol, FD&C Red #40 (Lake), FD&C Blue #2 (Lake), FD&C Yellow #5(Lake)).

Description:

One Natal RX Tablet is an orally administered prenatal/postnatal prescription folic acid-containing dietary supplement and should be administered under the supervision of a licensed medical practitioner.

DOSAGE AND ADMINISTRATION:

Before, during and/or after pregnancy, one tablet daily, with a meal, or as directed by a licensed healthcare practitioner regardless of lactation status.

WARNING:

Accidental overdose of iron-containing products is a leading cause of fatal poisoning in children under 6. Keep this product out of reach of children. In case of accidental overdose, call a doctor or poison control center immediately.

CAUTION:

High levels of folic acid may, especially in older adults, hide signs of Vitamin B-12 deficiency (such as pernicious anemia), a condition that can cause nerve damage.

Store at 15°-30° C (59°-86° F). Protect from light and moisture. Dispense in a tight, light-resistant container. Notice: Contact with moisture may produce surface discoloration or erosion.

Call your licensed medical practitioner about side effect. You may report side effects by calling 1-877-225-6999.

Manufactured for:

AARNA USA Inc.

Leland, NC 28451